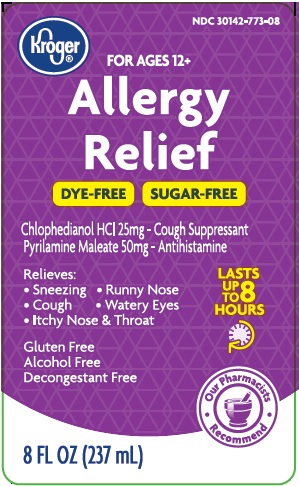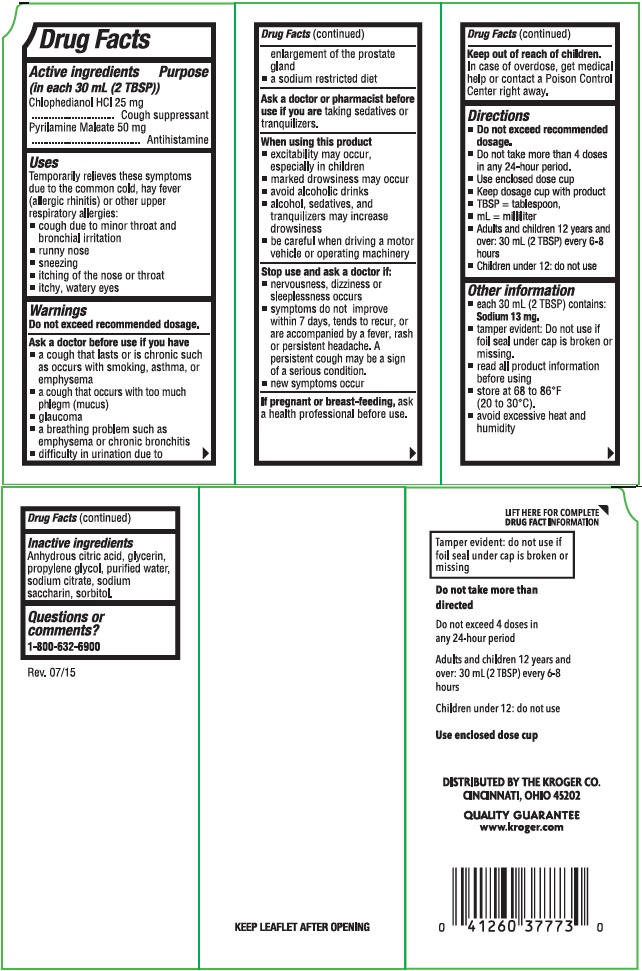 DRUG LABEL: Kroger Allergy Relief
NDC: 30142-773 | Form: LIQUID
Manufacturer: THE KROGER CO
Category: otc | Type: HUMAN OTC DRUG LABEL
Date: 20160630

ACTIVE INGREDIENTS: PYRILAMINE MALEATE 50 mg/30 mL; CHLOPHEDIANOL HYDROCHLORIDE 25 mg/30 mL
INACTIVE INGREDIENTS: ANHYDROUS CITRIC ACID; PROPYLENE GLYCOL; GLYCERIN; WATER; SODIUM CITRATE; SACCHARIN SODIUM; SORBITOL

Kroger Allergy Relief

Active ingredients

(in each 30 mL (2 TBSP))

Chlophedianol HCl 25 mg

Pyrilamine Maleate 50 mg

Purpose

Cough suppressant

Antihistamine

Uses

Temporarily relieves these symptoms due to the common cold, hay fever (allergic rhinitis) or other upper respiratory allergies:

- cough due to minor throat and bronchial irritation
- runny nose
- sneezing
- itching of the nose or throat
- itchy, watery eyes

Warnings

Do not exceed recommended dosage.

Ask a doctor before use if you have

- a cough that lasts or is chronic such as occurs with smoking, asthma, or emphysema
- a cough that occurs with too much phlegm (mucus)
- glaucoma
- a breathing problem such as emphysema or chronic bronchitis
- difficulty in urination due to enlargement of the prostate gland
- a sodium restricted diet

Ask a doctor or pharmacist before use if you are taking sedatives or tranquilizers.

When using this product

- excitability may occur, especially in children
- marked drowsiness may occur
- avoid alcoholic drinks
- alcohol, sedatives, and tranquilizers may increase drowsiness
- be careful when driving a motor vehicle or operating machinery

Stop use and ask a doctor if:

- nervousness, dizziness or sleeplessness occurs
- symptoms do not improve within 7 days, tends to recur, or are accompanied by a fever, rash or persistent headache. A persistent cough may be a sign of a serious condition.
- new symptoms occur

PREGNANCY OR BREAST FEEDING

If pregnant or breast-feeding, ask a health professional before use.

Keep out of reach of children.

In case of overdose, get medical help or contact a Poison Control Center right away.

Directions

- Do not exceed recommended dosage.
- Do not take more than 4 doses in any 24-hr period.
- Use enclosed dose cup
- Keep dosage cup with product
- TBSP=tablespoon
- mL=milliliter
- Adults and children 12 years and over: 30 mL (2 TBSP) every 6-8 hours
- Children under 12: do not use

Other information

- each 30 mL (2 TBSP) contains: Sodium 13 mg
- tamper evident: Do not use if foil seal under cap is broken or missing
- read all product information before using
- store at 68° to 86°F (20° to 30°C).
- avoid excessive heat and humidity

Inactive ingredients

Anhydrous citric acid, glycerin, propylene glycol, purified water, sodium citrate, sodium saccharin, sorbitol.

Questions or comments?

1-800-632-6900